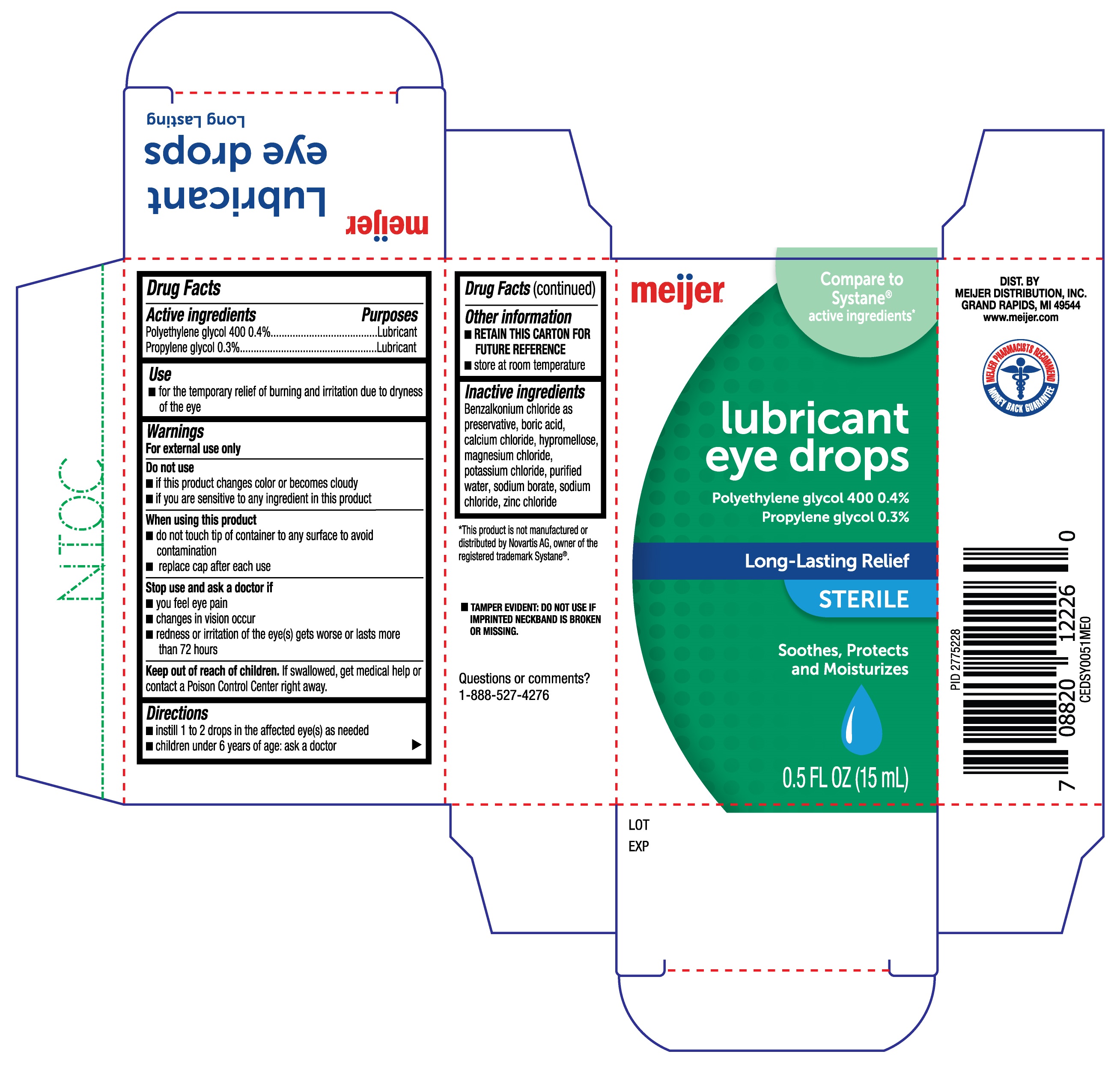 DRUG LABEL: Meijer Lubricant Eye Drops
NDC: 41250-319 | Form: SOLUTION/ DROPS
Manufacturer: Meijer Distribution, Inc.
Category: otc | Type: HUMAN OTC DRUG LABEL
Date: 20231222

ACTIVE INGREDIENTS: PROPYLENE GLYCOL 0.3 g/100 mL; POLYETHYLENE GLYCOL 400 0.4 g/100 mL
INACTIVE INGREDIENTS: CALCIUM CHLORIDE; HYPROMELLOSE, UNSPECIFIED; MAGNESIUM CHLORIDE; POTASSIUM CHLORIDE; SODIUM CHLORIDE; ZINC CHLORIDE; BENZALKONIUM CHLORIDE; SODIUM BORATE; BORIC ACID; WATER

Meijer Lubricant Eye Drops 15mL

Active ingredients

Polyethylene glycol 400 0.4%

Propylene glycol 0.3%

Purposes

Lubricant

Lubricant

Use

- for the temporary relief of burning and irritation due to dryness of the eye

Warnings

for external use only

Do not use

- if this product changes color or becomes cloudy
- if you are sensative to any ingredient in this product

When using this product

- do not touch tip of container to any surface to avoid contamination
- replace cap after each use

Stop use and ask a doctor if

- you feel eye pain
- changes in vision occur
- redness or irritation of the eye(s) gets worse or lasts more than 72 hours

Keep out of reach of children.

If swallowed, get medical help or contact a Poison Control Center right away.

Directions

- instill 1 to 2 drops in the affected eye(s) as needed
- children under 6 years of age: ask a doctor

Other information

- RETAIN THIS CARTON FOR FUTURE USE
- store at room temperature

Inactive ingredients

Benzalkonium chloride as a preservative, boric acid, calcium chloride, hypromellose, magnesium chloride, potassium chloride, purified water, sodium borate, sodium chloride, zinc chloride.